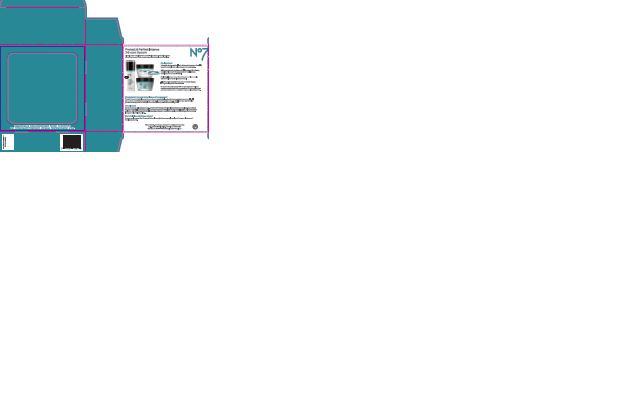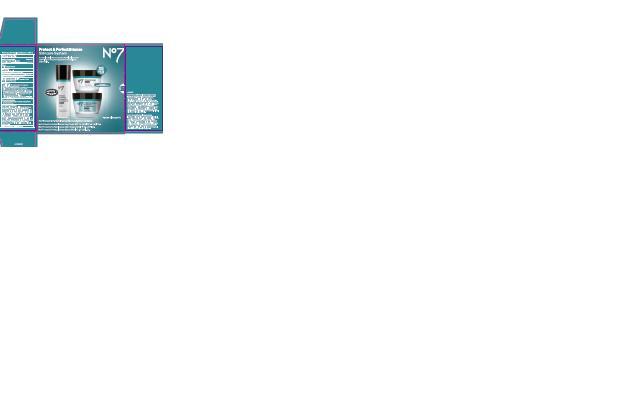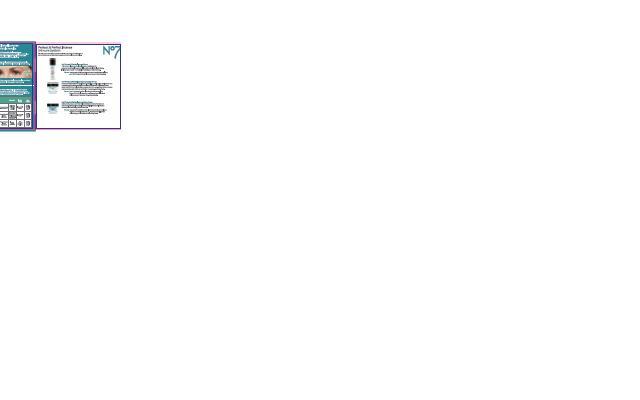 DRUG LABEL: No7 Protect and Perfect Intense Day Cream Sunscreen Broad Spectrum SPF 15
NDC: 65310-002 | Form: CREAM
Manufacturer: Packaging Systems LLC
Category: otc | Type: HUMAN OTC DRUG LABEL
Date: 20121219

ACTIVE INGREDIENTS: Avobenzone 1.5 g/50 g; Octocrylene 2 g/50 g; Octisalate 1 g/50 g
INACTIVE INGREDIENTS: Water; Glycerin; ALKYL (C12-15) BENZOATE; Dimethicone; CETEARYL GLUCOSIDE; ALUMINUM STARCH OCTENYLSUCCINATE; Tribehenin; AMMONIUM ACRYLOYLDIMETHYLTAURATE/VP COPOLYMER; Phenoxyethanol; Alcohol; SHEA BUTTER; POTASSIUM CETYL PHOSPHATE; CETOSTEARYL ALCOHOL; Butylene glycol; methylparaben; Xanthan gum; ETHYLPARABEN; DIPROPYLENE GLYCOL; VITAMIN A PALMITATE; ASCORBYL GLUCOSIDE; HYALURONATE SODIUM; ALFALFA; EDETATE SODIUM; TERT-BUTYL ALCOHOL; LUPINUS ALBUS SEED; PHYLLANTHUS EMBLICA FRUIT; polysorbate 20; potassium hydroxide; ginkgo; ethylhexylglycerin; tocopherol; PALMITOYL OLIGOPEPTIDE; PALMITOYL TETRAPEPTIDE-7

No7 Protect and Perfect Intense Day Sunscreen Broad Spectrum SPF 15 - Skincare System

ACTIVE INGREDIENT

Active Ingredients Avobenzone 3.0%, Octisalate 2%, Octocrylene 4%

Purpose Sunscreen

PURPOSE

Uses helps prevent sunburn

Warnings

For external use only

Do not use on damaged or broken skin

When using this product keep out if eyes. Rinse with water to remove.

Stop use and ask a doctor if rash occurs.

Keep out of reach of children. If swallowed get medical help or contact a poison control center right away.

Directions

Apply liberally 15 minutes before sun exposure

Use a water resistant sunscreen if swimming or sweating

Reapply at least every 2 hours

Chidren under 6 months of age: Ask a doctor

Sun Protection Measures

Spending time in the sun increases your risk of skin cancer and early skin aging. To decrease this risk, regularly use a sunscreen with a broad spectrum SPF value of 15 or higher and other sun protection measures including:

limit time in the sun, especially from 10a,m - 2p.m

wear long-sleeved shirts, pants, hats, and sunglasses

Other information

Protect the product in this container from excessive heat and direct sun

Inactive Ingredients

Aqua (water), Glycerin, C12-15 alkyl benzoate, Dimethicone, Cetearyl glucoside, Aluminum starch octenylsuccinate, Tribehenin, Ammonium acryloyldimethyltaurate/VP copolymer, phenoxyethanol, Alcohol denat.,Butyrospermum parkii (Shea) butter, Potassium cetyl phosphate, Cetearyl alcohol, Butylene glycol, Dimethiconol, Methylparaben, Parfum (Fragrance), Xanthan gum, Ethylparaben, Dipropylene glycol, Retinyl palmitate, Ascorbyl glucoside, Sodium hyaluronate, Medicago sativa (Alfalfa) extract, Tetrasodium EDTA, T-butyl alcohol, Lupinus albus seed extract, Carbomer, Phyllanthus emblica fruit extract, Dimethylmethoxy chromanol, Polysorbate 20, Potassium hydroxide, Ginkgo biloba leaf extract, Ethylhexylglycerin, Simethicone, Tocopherol, Palmitoyl oligopeptide, Palmitoyl tetrapeptide-7

USA: Questions? 1-866-75-BOOTS

Ingredients continued

No7 Protect and Perfect Intense Night Cream

Ingredients:

Aqua(Water), Glycerin, Butyrospermum parkii(Shea) butter, PPG-15 stearyl ether, Sorbitan stearate, Dimethicone, Cetearyl alcohol, Ethylhexyl stearate, Polyacrylamide, Phenoxyethanol, C13-14 isoparaffin, C18-36 acid glycol ester, Alcohol denat., Butylene glycol, Dimethiconol, Sucrose cocoate, Parfum (Fragrance), Methylparaben, Carbomer, Laureth-7, Ethylparaben, Dipropylene glycol, Retinyl palmitate, Xanthan gum, Sodium hyaluronate, Ascorbyl glucoside, Medicago sativa (Alfalfa) extract, Tetrasodium EDTA, POtassium hydroxide, Lupinus albus seed extract, Phyllanthus emblica fruit extract, Dimethylmethoxy chromanol, Polysorbate 20, Ginkgo biloba leaf extract, Ethylhexylglycerin, BHT, Tocopherol, Palmitoyl oligopeptide, Palmitoyl tetrapeptide-7

No7 Protect and Perfect Intense Serum

Ingredients:

Cyclopentasiloxane, Aqua(Water), Butylene glycol, Dimethicone crosspolymer, Cyclohexasiloxane, Glycerin, Sodium ascorbyl phosphate, Arabinogalactan,Magnesium sulfate, PEG/PPG-18/18 Dimethicone, Phenoxyethanol, Sodium PCA, Cetyl PEG/PPG-10/dimethicone, Polyglyceryl-4 isostearate, Hexyl laurate, Retinyl palmitate, Medicago sativa (Alfalfa) extract, Methylparaben, Propylene glycol, Ethylparaben, Lupinus albus seed extract, Carbomer, Polysorbate 20, Panax ginseng root extract, Ethylhexylglycerin, Morus alba leaf extract, Tocopherol,

Palmitoyl oligopeptide, Palmitoyl tetrapeptide-7

DESCRIPTION

Protect and Perfect Intense Skincare System

Clinically proven technology from our best-selling serum now formulated into a day and night cream for improving the appearance of deep lines and wrinkles.

Key Ingredients:

Vitamin C, Gingko and Emblica Fruit Extract (Antioxidant Complex) target free radicals that can lead to premature skin aging.

White Lupin Extract, Peptides and Alfalfa Extract (Skin Firming Complex) help smooth the appearance of deep lines and wrinkles and firm the skin's surface.

Pro-Retinol works at the surface of the skin to help normalize skin renewal, leaving skin looking smoother

Glycerin and Shea Butter moisturize and nourish the skin, leaving it feeling softer and smoother

Sunscreen Broad Spectrum SPF 15 in the Day Cream helps to provide protection against the aging effects of the sun when used as directed with other sun protection measures - see Drug Facts.

What is the No7 Protect and Perfect Intense Skincare System ?

The No7 Protect and Perfect Intense Skincare System is a rich and luxurious skincare system containing our clinically proven serum, a renewing day cream and an intensively nourishing night cream. This daily skincare regimen helps you smooth the appearance of deep lines and wrinkles and promotes firmer feeling skin.

How do I use it ?

Use as part of your daily skincare routine. Smooth No7 Protect and Perfect Intense Serum onto a clean face and neck with your finger tips. In the morning, follow with No7 Protect and Perfect Intense Day Cream. At night, follow your serum application with No7 Protect and Perfect Intense Night Cream to moisturize and help improve the appearance of deep lines and wrinkles while you sleep.

What should I use with these products ?

For best results use with No7 Protect and Perfect Intense Eye Cream, specially developed for deeper lines around the delicate eye area.

To use:

No7 Protect and Perfect Intense Serum

Use day and night. Smooth onto face and neck before applying your No7 Protect and Perfect Intense Day and Night Creams

No7 Protect and Perfect Intense Day Cream SPF 15
Use in the morning after cleansing the skin and applying Protect and Perfect Intense Serum. Massage in small upward circles over your face and neck. Avoid eye area.

No7 Protect and Perfect Intense Night Cream

Use just before bedtime, after cleansing the skin and applying Protect and Perfect Intense Serum. Massge in small upward circles over your face and neck. Avoid eye area.

PATIENT COUNSELING INFORMATION

Made in the UK. The Boots Company PLC Nottingham England NG2 3AA
Dist. by Boots Retail USA Inc. Norwalk CT 06851 USA
Questions? 1-866-75-Boots/www.shopbootsusa.com

DESCRIPTION

Clinically proven

Visible results

No7 Protect and Perfect Intense Serum

Improves the appearance of deep lines and wrinkles with regular use. It immediately improves skin's radiance after the first application.

Pro-retinol works at the surface of the skin to help normalize skin renewal, leaving skin looking smoother.

The appearance of deep lines and wrinkles are reduced, leaving skin lookng younger in just 4 weeks.

No7 Protect and Perfect Intense Skincare System

Experience a range formulated to work even better together to smooth the appearance of deep lines and wrinkles and promote firmer feeling skin.

 | Key Benefits | Instant; Benefits | After; 4 weeks
Protect and Perfect Intense Serum | Directly targets the appearance of deep lines and wrinkles | Improves skin’s radiance | Deep lines and wrinkles are visibly reduced
Protect and Perfect Intense Day Cream | Sunscreen Broad Spectrum SPF 15 decreases the risk of early skin aging if used as directed – see Drug Facts | Improves skin’s texture | Deep lines and wrinkles are visibly reduced
No7 Protect and Perfect Intense Night Cream | Intensive overnight moisturization | Skin is moisturized and feels more supple | Deep lines and wrinkles are visibly reduced

Jar

Active ingredients: Avobenzone 3%, Octisalate 2.%, Octocrylene 4%

warning

JAR TEXT

Warning: Avoid contact with eyes. If product gets into the eyes rinse well with water immediately.

DESCRIPTION

JAR TEXT

Smooth into your face and neck after applying your No7 serum.

PATIENT COUNSELING INFORMATION

JAR TEXT

The Boots Company PLC

Nottingham England NG2 3AA
Dist. by Boots Retail USA Inc.

Norwalk CT 06851 USA
Made in the UK
www.Boots.com

PACKAGE LABEL

carton